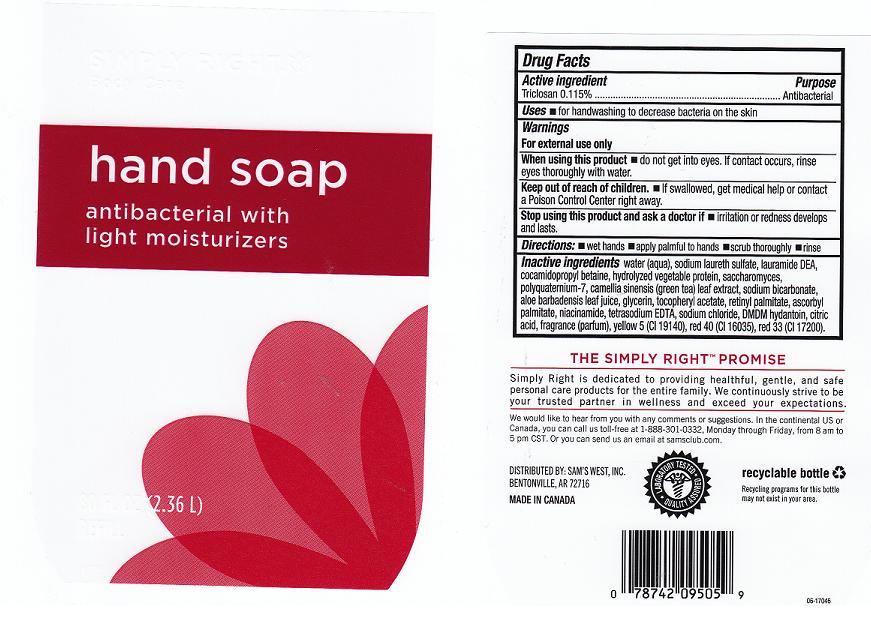 DRUG LABEL: ANTIBACTERIAL  
NDC: 68196-142 | Form: LIQUID
Manufacturer: SAM'S WEST INC.
Category: otc | Type: HUMAN OTC DRUG LABEL
Date: 20110606

ACTIVE INGREDIENTS: TRICLOSAN 0.115 L/100 L
INACTIVE INGREDIENTS: WATER; SODIUM LAURETH SULFATE; LAURIC DIETHANOLAMIDE; COCAMIDOPROPYL BETAINE; SOY PROTEIN; SACCHAROMYCES LYSATE; POLYQUATERNIUM-7 (70/30 ACRYLAMIDE/DADMAC; 1600 KD); GREEN TEA LEAF; SODIUM BICARBONATE; ALOE VERA LEAF; GLYCERIN; .ALPHA.-TOCOPHEROL ACETATE, D-; VITAMIN A PALMITATE; ASCORBYL PALMITATE; NIACINAMIDE; EDETATE SODIUM; SODIUM CHLORIDE; DMDM HYDANTOIN; ANHYDROUS CITRIC ACID; FD&C YELLOW NO. 5; FD&C RED NO. 40; D&C RED NO. 33

DRUG FACTS

ACTIVE INGREDIENT

TRICLOSAN 0.115 PERCENT

PURPOSE

ANTIBACTERIAL

USES

FOR HANDWASHING TO DECREASE BACTERIA ON THE SKIN.

WARNINGS

FOR EXTERNAL USE ONLY.

WHEN USING THIS PRODUCT

DO NOT GET INTO EYES. IF CONTACT OCCURS, RINSE EYES THOROUGHLY WITH WATER.

KEEP OUT OF REACH OF CHILDREN.

IF SWALLOWED, GET MEDICAL HELP OR CONTACT A POISON CONTROL CENTER RIGHT AWAY.

STOP USING THIS PRODUCT AND ASK A DOCTOR IF

IRRITATION OR REDNESS DEVELOPS AND LASTS.

DIRECTIONS:

- WET HANDS
- APPLY PALMFUL TO HANDS
- SCRUB THOROUGHLY
- RINSE

INACTIVE INGREDIENTS

WATER, SODIUM LAURETH SULFATE, LAURAMIDE DEA, COCAMIDOPROPYL BETAINE, HYDROLYZED VEGETABLE PROTEIN, SACCHAROMYCES, POLYQUATERNIUM-7, CAMELLIA SINENSIS (GREEN TEA) LEAF EXTRACT, SODIUM BICARBONATE, ALOE BARBADENSIS LEAF JUICE, GLYCERIN, TOCOPHERYL ACETATE, RETINYL PALMITATE, ASCORBYL PALMITATE, NIACINAMIDE, TETRASODIUM EDTA, SODIUM CHLORIDE, DMDM HYDANTOIN, CITRIC ACID, FRAGRANCE, YELLOW 5 (CI 19140), RED 40 (CI 16035), RED 33 (CI 17200).